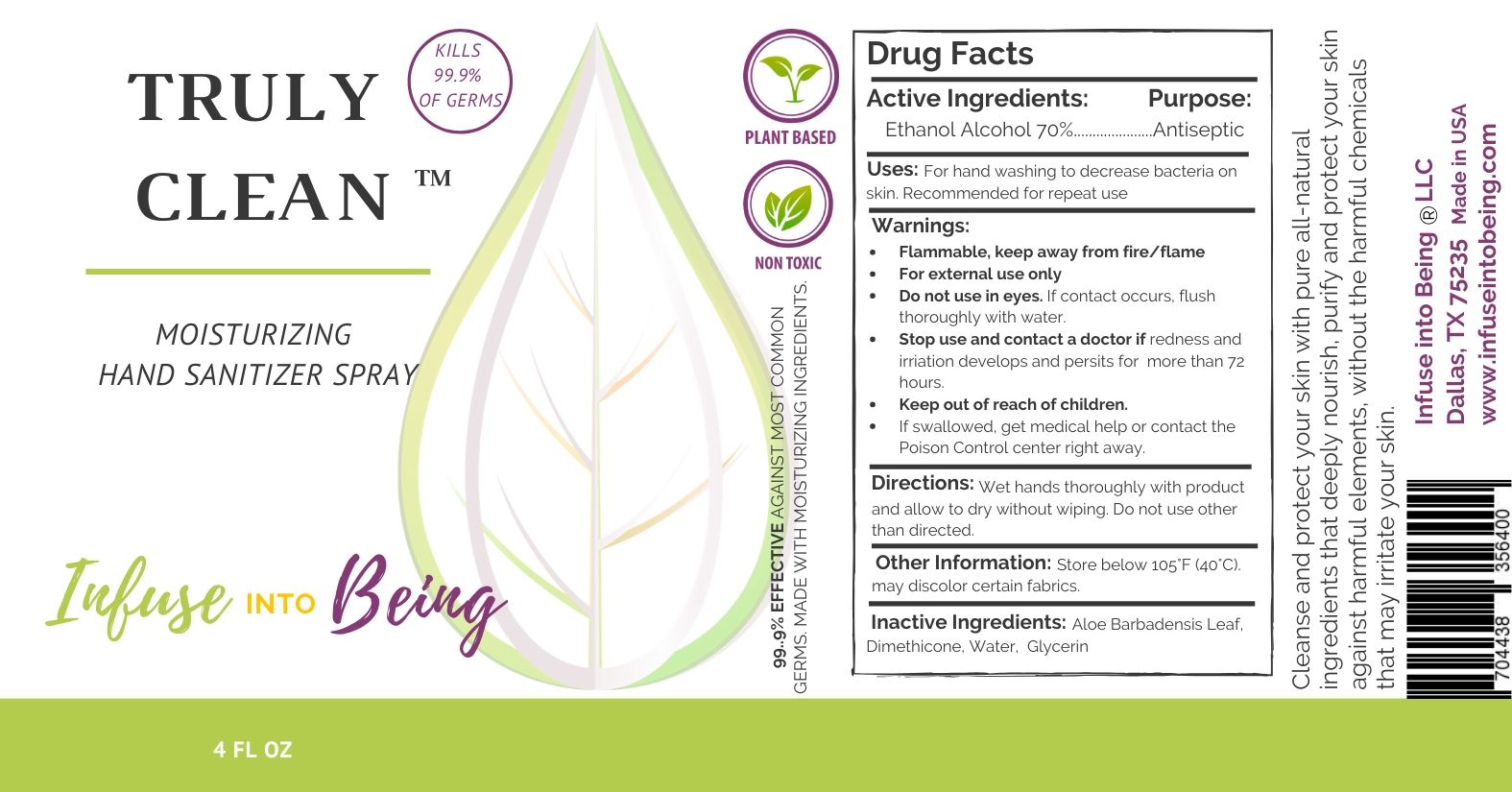 DRUG LABEL: Truly Clean
NDC: 78022-101 | Form: SPRAY
Manufacturer: Infuse into Being LLC
Category: otc | Type: HUMAN OTC DRUG LABEL
Date: 20200526

ACTIVE INGREDIENTS: ALCOHOL 70 mL/100 mL
INACTIVE INGREDIENTS: GLYCERIN; ALOE VERA LEAF; WATER; Dimethicone

Infuse into Being Truly Clean Moisturizing Hand Sanitizer Spray

Cleanse and protect your skin with pure all-natural ingredients that deeply nourish, purify and protect your skin against harmful elements, without the harmful chemicals that may irritate your skin.

Active Ingredients

Ethanol Alcohol 70%

Purpose

Antiseptic

Use

For hand washing to decrease bacteria on skin. Recommended for repeat use.

Warnings

Flammable, keep away from fire/flame
For external use only

Do not use in eyes. If contact occurs, flush thoroughly with water.

Stop use and contact a doctor if redness and irriation develops and persits for more than 72 hours.

Keep out of reach of children. If swallowed, get medical help or contact the Poison Control center right away.

Directions

Wet hands thoroughly with product and allow to dry without wiping. Do not use other than directed.

Other information

- Store below 105°F (40°C). may discolor certain fabrics.

Inactive ingredients

Aloe Barbadensis Leaf, Dimethicone, Water, Glycerin

Package Label - Principal Display Panel

4 FL OZ NDC: 78022-101-04